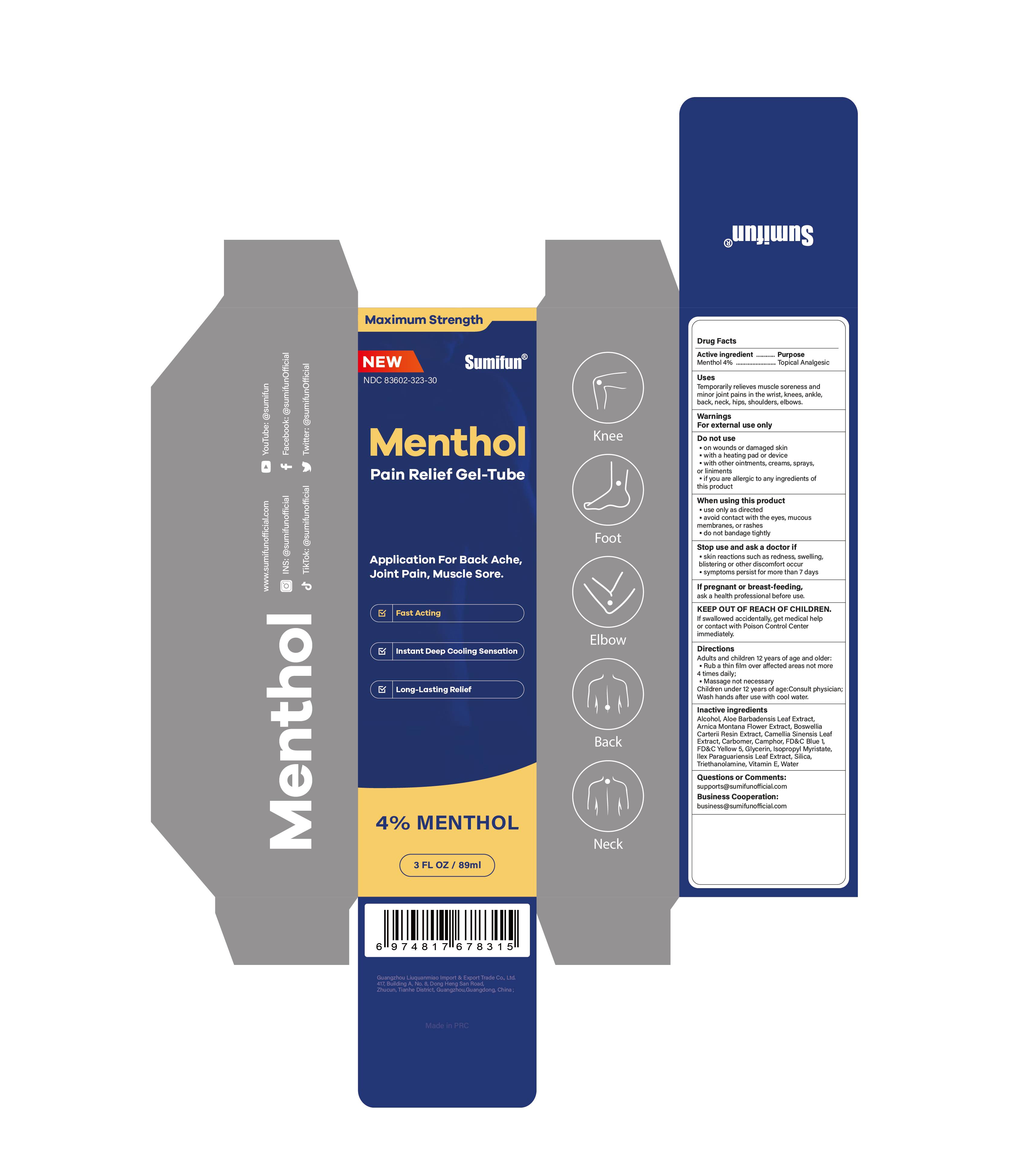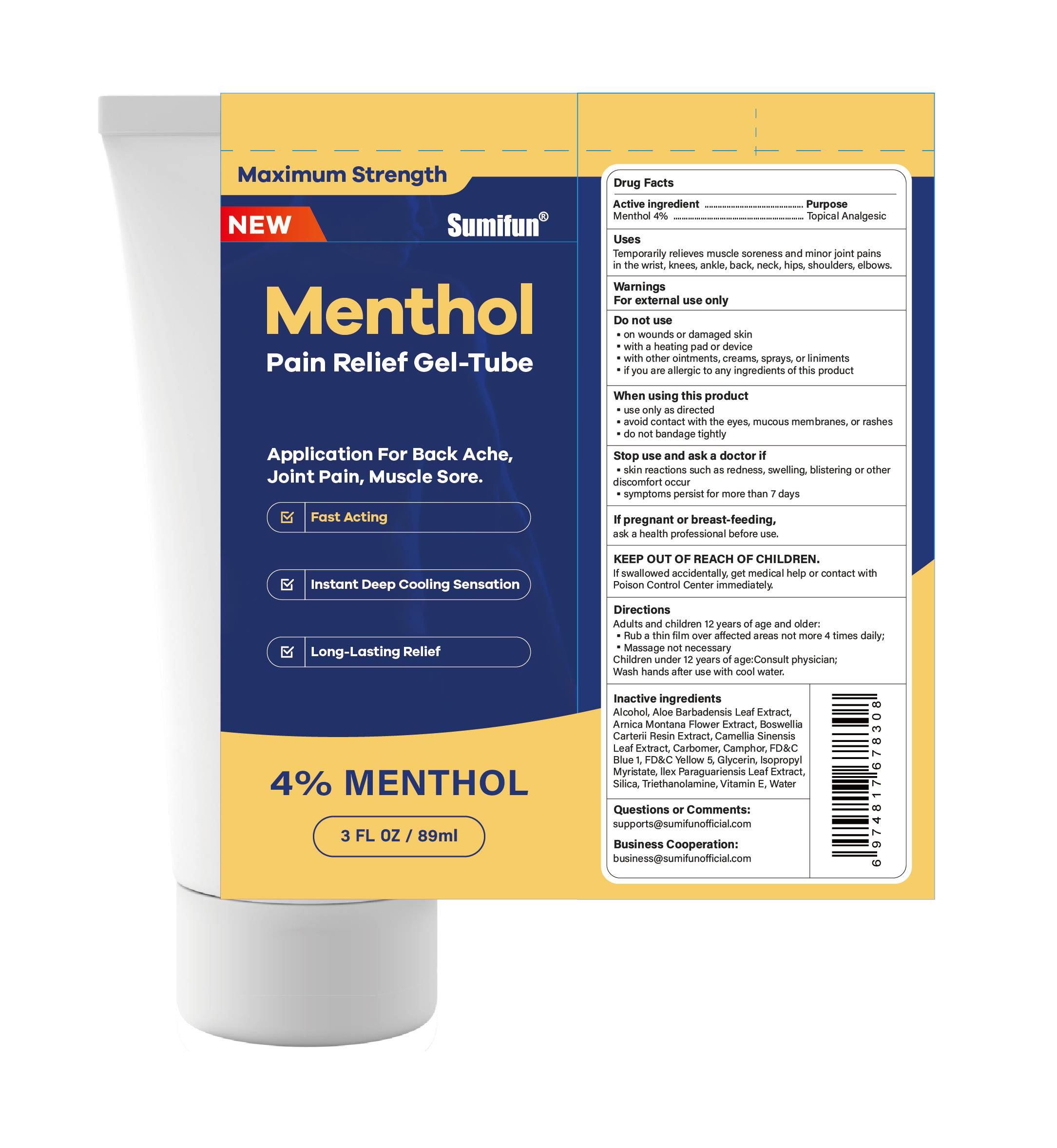 DRUG LABEL: Menthol Pain Relief Gel-Tube
NDC: 83602-323 | Form: GEL
Manufacturer: Guangzhou Liuquanmiao Import & Export Trade Co., Ltd.
Category: otc | Type: HUMAN OTC DRUG LABEL
Date: 20250207

ACTIVE INGREDIENTS: MENTHOL 0.04 g/1 mL
INACTIVE INGREDIENTS: ALCOHOL 95%; TROLAMINE; WATER; SILICON DIOXIDE; ILEX PARAGUARIENSIS LEAF; ISOPROPYL MYRISTATE; .ALPHA.-TOCOPHEROL, D-; ALOE VERA LEAF; GLYCERIN; FD&C YELLOW NO. 5; FD&C BLUE NO. 1; GREEN TEA LEAF; CARBOMER HOMOPOLYMER, UNSPECIFIED TYPE; FRANKINCENSE; ARNICA MONTANA FLOWER; CAMPHOR (SYNTHETIC)

Liuquanmiao, Menthol Pain Relief Gel-Tube, 3.0 fl. oz / 89 mL, Gel, Tube

Active ingredient

Menthol 4% ...... Purpose: Topical Analgesic

Purpose

Topical Analgesic

Uses

Temporarily relieves muscle soreness and minor joint pains in the wrist, knees, ankle, back, neck, hips, shoulders, elbows.

Warnings

For external use only

Do not use

• on wounds or damaged skin

• with a heating pad or device

• with other ointments, creams, sprays, or liniments

• if you are allergic to any ingredients of this product

When using this product

• use only as directed

• avoid contact with the eyes, mucous membranes, or rashes

• do not bandage tightly

Stop use ... if

• skin reactions such as redness, swelling, blistering or other discomfort occur

• symptoms persist for more than 7 days

... ask a doctor if

• skin reactions such as redness, swelling, blistering or other discomfort occur

• symptoms persist for more than 7 days

If pregnant or breast-feeding,

Ask a health professional before use.

KEEP OUT OF REACH OF CHILDREN.

If swallowed accidentally, get medical help or contact with Poison Control Center immediately.

Directions

Adults and children 12 years of age and older:

• Rub a thin film over affected areas not more than 4 times daily;

• Message not necessary

Children under 12 years of age: Consult physician.

Wash hands after use with cool water.

Inactive ingredients

Alcohol, Aloe Barbadensis Leaf Extract, Arnica Montana Flower Extract, Boswellia Carterii Resin Extract, Camellia Sinensis Leaf Extract, Carbomer, Camphor, FD&C Blue 1, FD&C Yellow 5, Glycerin, Isopropyl Myristate, Ilex Paraguariensis Leaf Extract, Silica, Triethanolamine, Vitamin E, Water

Questions or Comments:

supports@sumifunofficial.com